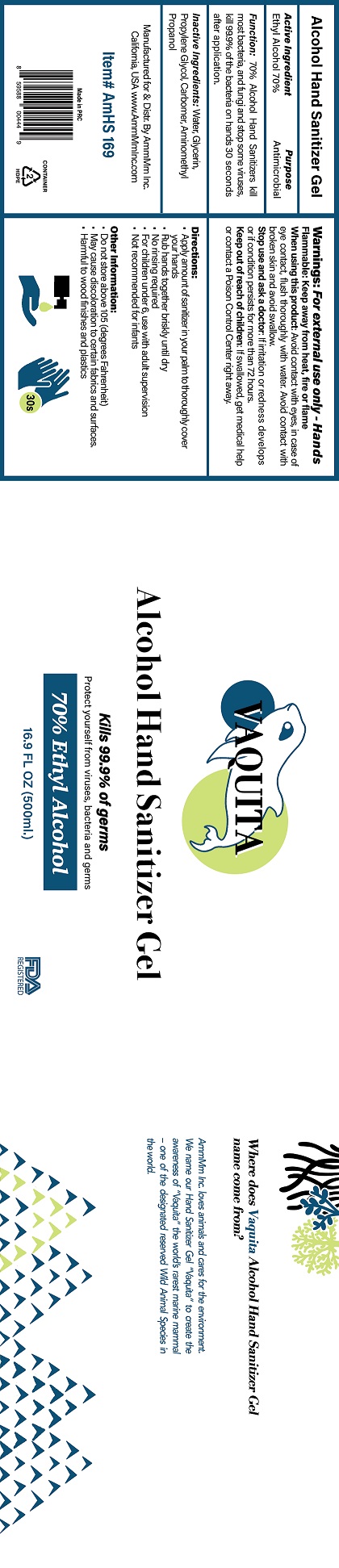 DRUG LABEL: BELLI MOISTURIZING HAND SANITIZER

NDC: 42281-101 | Form: LOTION
Manufacturer: ABT Belli-Materna Inc
Category: otc | Type: HUMAN OTC DRUG LABEL
Date: 20220106

ACTIVE INGREDIENTS: BENZALKONIUM CHLORIDE 0.1 g/100 mL
INACTIVE INGREDIENTS: WATER; ALCOHOL; POLYSORBATE 20; PEG-7 GLYCERYL COCOATE; CARBOMER INTERPOLYMER TYPE A (ALLYL SUCROSE CROSSLINKED); TROLAMINE; LEMON OIL

BELLI MOISTURIZING HAND SANITIZER - BKC 0.1% (4228-101)

ACTIVE INGREDIENT

BENZALKONIUM CHLORIDE 0.1%

PURPOSE

ANTIMICROBIAL

USES

- REDUCES BACTERIA ON THE SKIN

WARNINGS

WHEN USING THIS PRODUCT

- KEEP OUT OF EYES / RINSE WITH WATER TO REMOVE

STOP USE AND ASK A DOCTOR IF

- RASH OR SKIN ORRITATION DEVELOPS

KEEP OUT OF REACH OF CHILDREN.

IN CASE OF ACCIDENTAL INGESTION, CONTACT A POISON CONTROL CENTER IMMEDIATELY.

DIRECTIONS

- PLACE ENOUGH PRODUCT IN YOUR HANDS TO THOROUGHLY COVER YOUR HANDS AND RUB IN.

INACTIVE INGREDIENTS

WATER, SD ALCOHOL 40-B, POLYSORBATE 20, PEG-7 GLYCERYL COCOATE, ACRYLATES/C10-30 ALKYL ACRYLATE CROSSPOLYMER, TRIETHANOLAMINE, CITRUS LIMON (LEMON) PEEL OIL